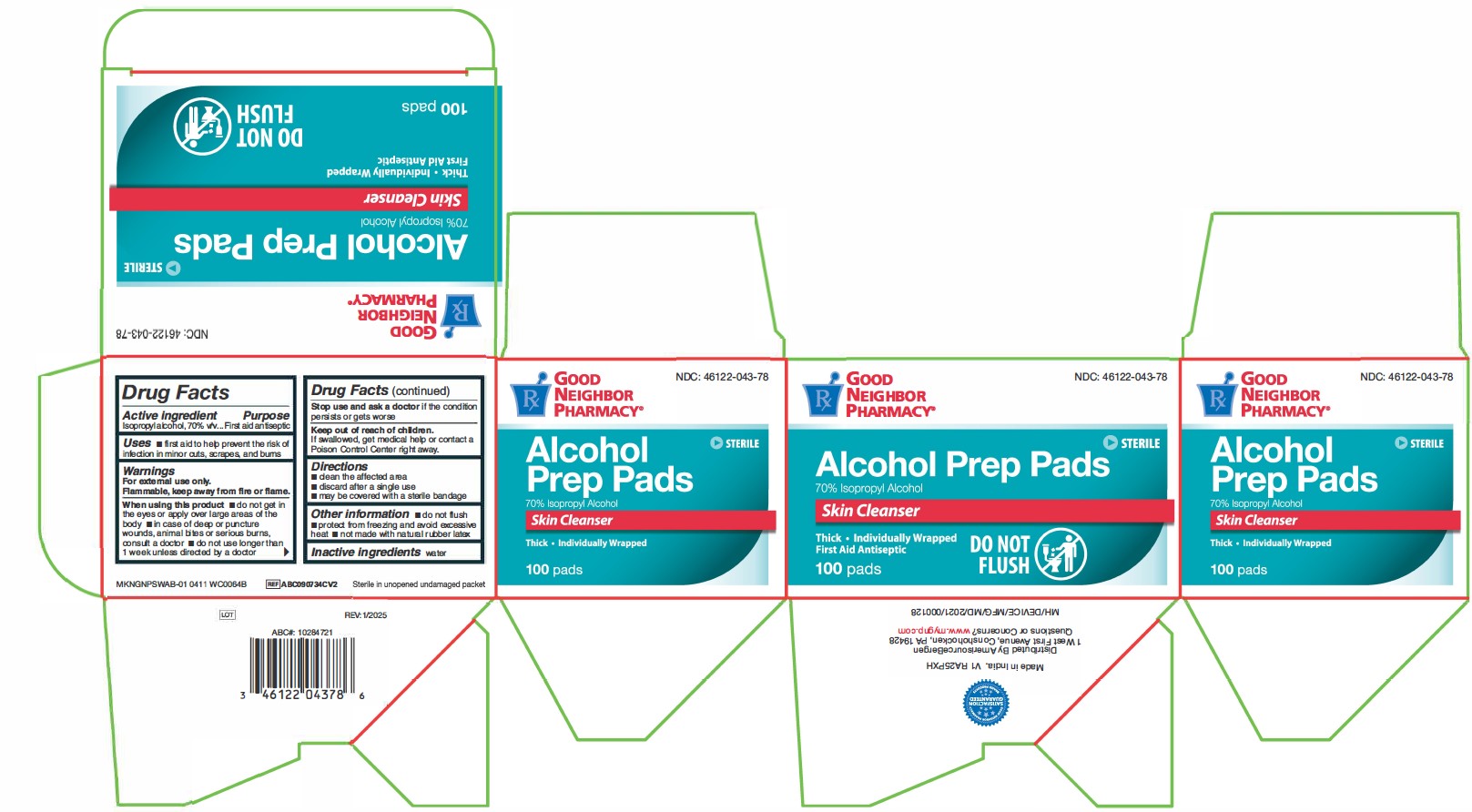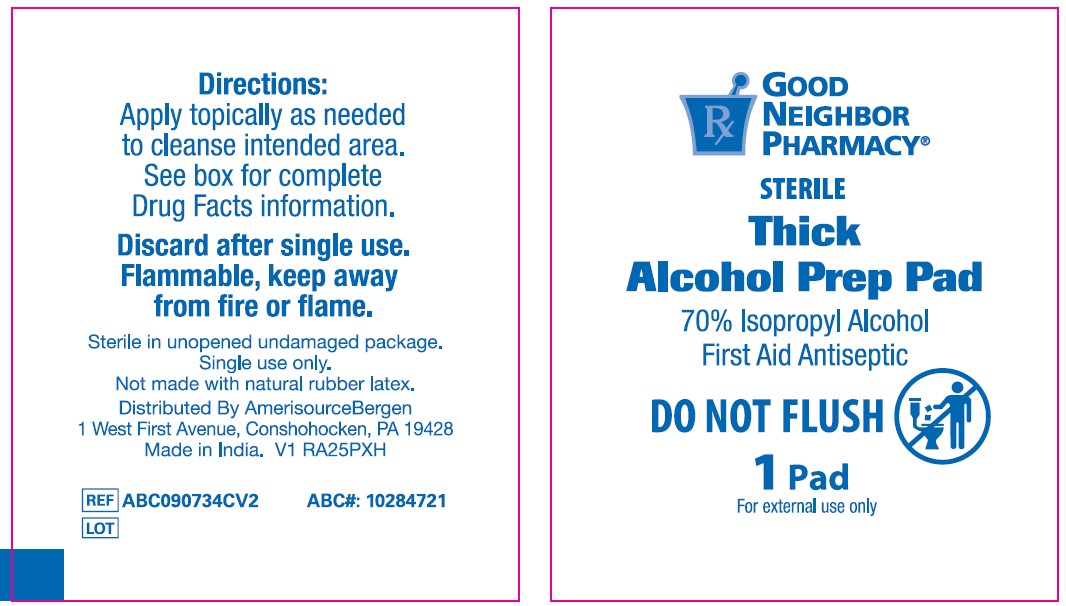 DRUG LABEL: Good Neighbor Pharmacy Alcohol Antiseptic Skin Cleanser
NDC: 46122-043 | Form: SWAB
Manufacturer: Amerisouce Bergen
Category: otc | Type: HUMAN OTC DRUG LABEL
Date: 20250624

ACTIVE INGREDIENTS: ISOPROPYL ALCOHOL 70 mL/100 mL
INACTIVE INGREDIENTS: WATER

46122-043 Amerisource Bergen 70% IPA Prep Pad

Active ingredient

Isopropyl alcohol 70% v/v

Purpose

First aid antiseptic

Uses

- first aid to help prevent the risk of infection in minor cuts, scrapes, and burns

Warnings

For external use only.

Flammable, keep away from fire or flame

When using this product

- do not get into eyes or apply over large areas of the body
- in case of deep or puncture wounds, animal bites or serious burns, consult a doctor
- do not use longer than 1 week unless directed by a doctor

Stop use and ask a doctor if

- if the condition persists or gets worse

Keep out of reach of children.

If swallowed, get medical help or contact a Poison Control Center right away.

Directions

- clean the affected area
- discard after single use
- may be covered with a sterile bandage

Other information

- do not flush
- protect from freezing and avoid excessive heat
- not made with natural rubber latex

Inactive ingredients

water

Manufacturing Information

Distributed by:

AmerisourceBergen

1 West First Avenue, Conshohocken, PA 19428

Made in China with components of Taiwan

www.mygnp.com

REF: ABC090734CV1

V3 RH23LPD